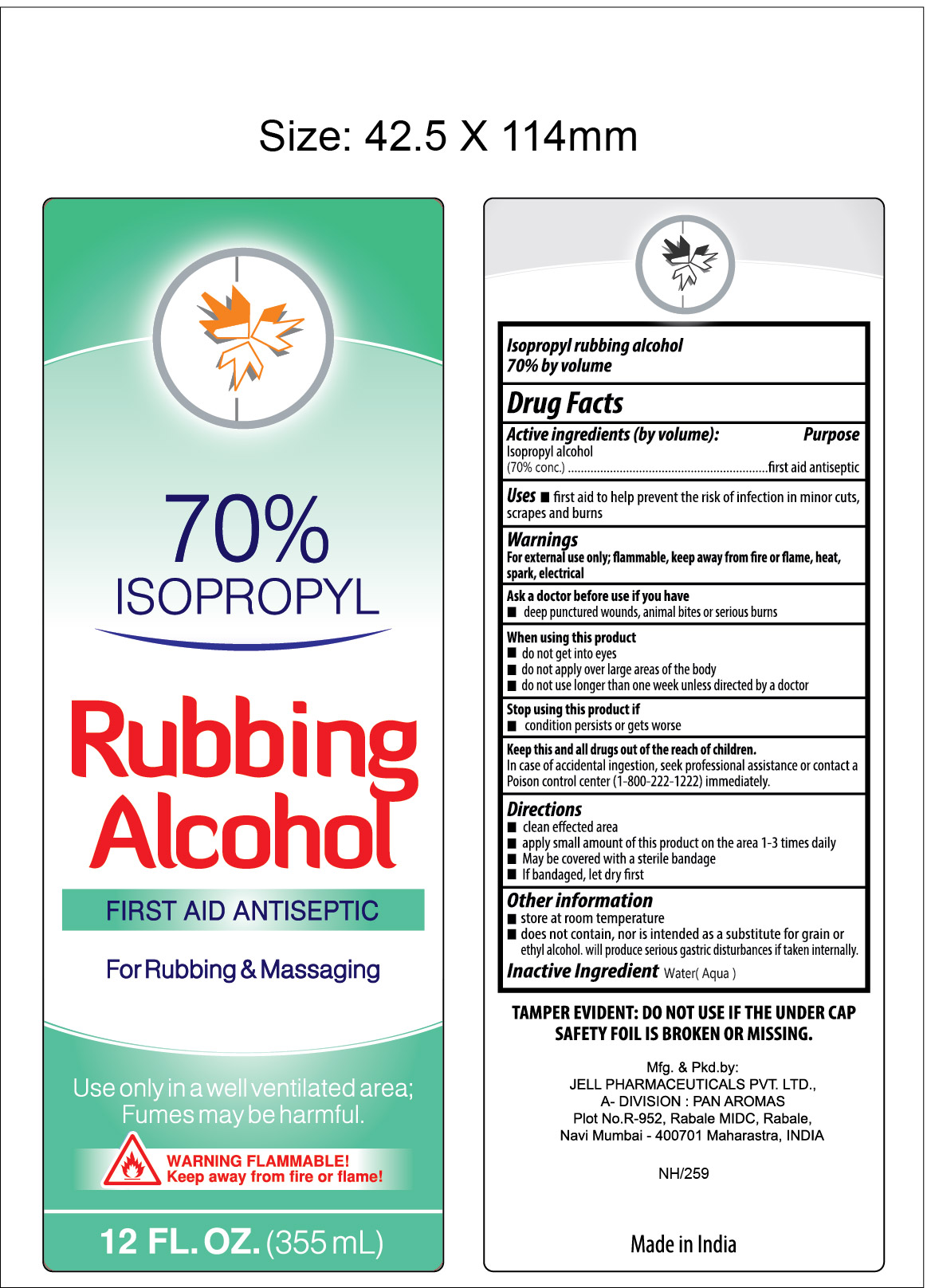 DRUG LABEL: Isopropyl Rubbing Alcohol 70%
NDC: 30400-504 | Form: LIQUID
Manufacturer: Jell Pharmaceuticals Pvt. Ltd.
Category: otc | Type: HUMAN OTC DRUG LABEL
Date: 20251111

ACTIVE INGREDIENTS: ISOPROPYL ALCOHOL 70 mL/100 mL
INACTIVE INGREDIENTS: WATER

Isopropyl Rubbing Alcohol 70%

Active Ingredients (by volume)

Isopropyl alcohol (70% conc.)

Purpose

First aid antiseptic

Uses

- first aid to help prevent the risk of infection in minor cuts, scrapes and burns

Warnings

For external use only; flammable, keep away from fire or flame, heat, spark, electrical

Ask a doctor before use if you have

- deep punctured wounds, animal bites or serious burns

When using this product

- do not get into eyes
- do not apply over large areas of the body
- do not use longer than one week unless directed by a doctor

Stop using this product if

- condition persists or gets worse

KEEP OUT OF REACH OF CHILDREN

Keep this and all drugs out of the reach of children

In case of accidental ingestion, seek professional assistance or contact a Poison control center (1-800-222-1212) immediately

Directions

- clean effected area
- apply small amount of this product on the area 1-3 times daily
- may be covered with a sterile bandage
- if bandaged, let dry first

Other information

- store at room temperature
- does not contain, nor is intended as a substitute for grain or ethyl alcohol
- will produce serious gastric disturbance if taken internally

Inactive ingredient

Water(Aqua)

PRINCIPAL DISPLAY PANEL

ISOPROPYL RUBBING ALCOHOL 70%
FIRST AID ANTISEPTIC
12 FL.OZ (355 mL)